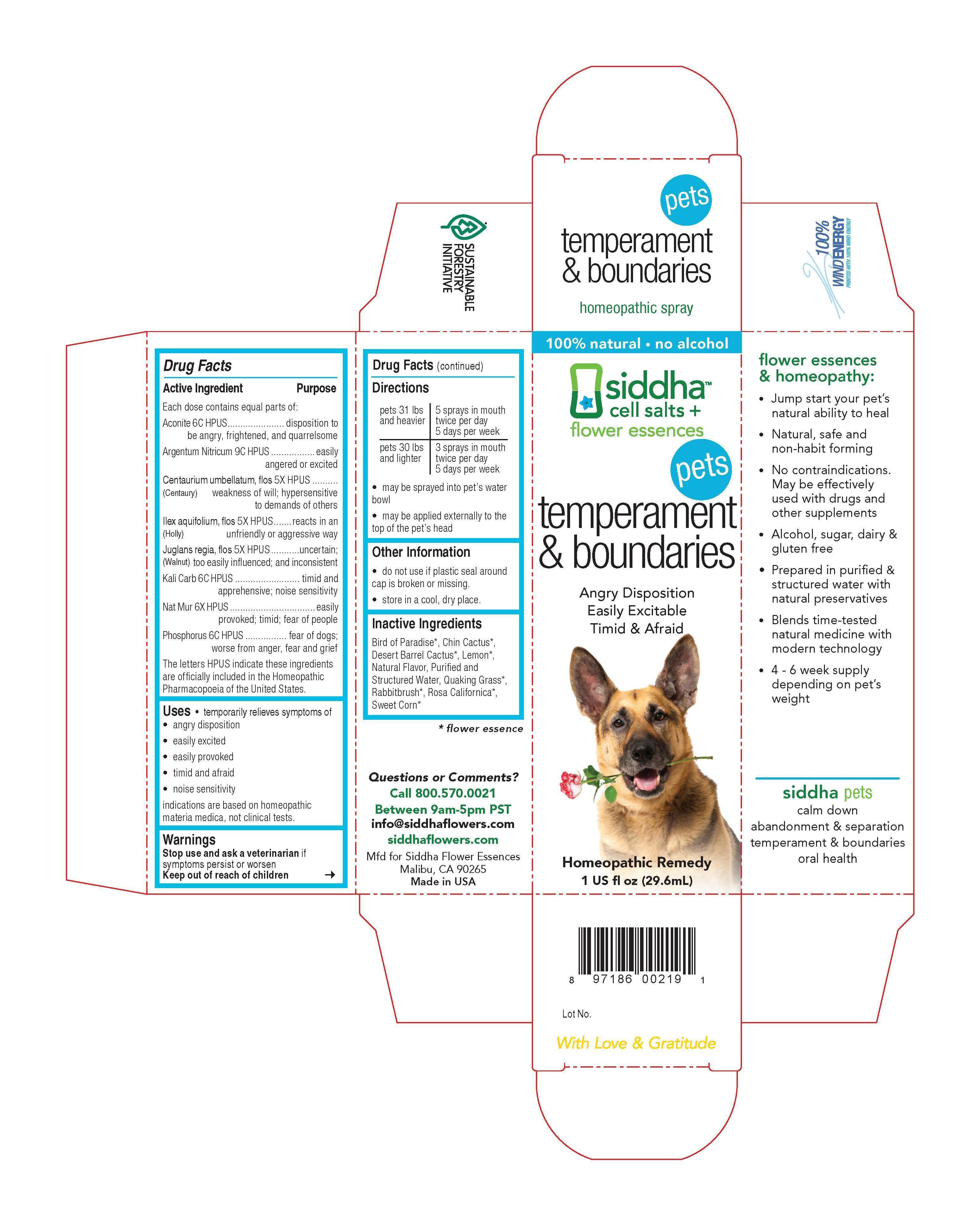 DRUG LABEL: temperament and boundaries
NDC: 69779-024 | Form: SPRAY
Manufacturer: Siddha Flower Essences LLC
Category: homeopathic | Type: OTC ANIMAL DRUG LABEL
Date: 20150409

ACTIVE INGREDIENTS: ACONITUM NAPELLUS 6 [hp_C]/29.6 mL; SILVER NITRATE 9 [hp_C]/29.6 mL; CENTAURIUM ERYTHRAEA FLOWER 5 [hp_X]/29.6 mL; ILEX AQUIFOLIUM FLOWERING TOP 5 [hp_X]/29.6 mL; JUGLANS REGIA FLOWERING TOP 5 [hp_X]/29.6 mL; POTASSIUM CARBONATE 6 [hp_C]/29.6 mL; SODIUM CHLORIDE 6 [hp_X]/29.6 mL; PHOSPHORUS 6 [hp_C]/29.6 mL
INACTIVE INGREDIENTS: LEMON; WATER

Drug Facts

Active Ingredient

Each dose contains equal parts of:

Aconite 6C HPUS
Argentum Nitricum 9C HPUS
Centaurium umbellatum, flos (Centaury) 5X HPUS
Ilex aquifolium, flos (Holly) 5X HPUS
Juglans regia, flos (Walnut) 5X HPUS
Kali Carb 6C HPUS
Nat Mur 6X HPUS
Phosphorus 6C HPUS

Purpose

Each dose contains equal parts of:
Aconite 6C HPUS.............................................................disposition to be angry, frightened, and quarrelsome
Argentum Nitricum 9C HPUS..........................................easily angered or excited
Centaurium umbellatum, flos (Centaury) 5X HPUS........weakness of will; hypersensitive to demands of others
Ilex aquifolium, flos (Holly) 5X HPUS..............................reacts in any unfriendly or aggressive way
Juglans regia, flos (Walnut) 5X HPUS.............................uncertain; too easily influenced, and inconsistent
Kali Carb 6C HPUS..........................................................timid and apprehensive; noise sensitivity
Nat Mur 6X HPUS.............................................................easily provoked; timid; fear of people
Phosphorus 6C HPUS.......................................................fear of dogs; worse from anger, fear and grief
The letters HPUS indicate these ingredients are officially included in the Homeopathic Pharmacopoeia of the United States.

Uses

- temporarily relieves symptoms of
- angry disposition
- easily excited
- easily provoked
- timid and afraid
- noise sensitivity

indications are based on homeopathic materia medica, not clinical tests.

Warnings

Stop use and ask a veterinarian if symptoms persist or worsen

Keep out of reach of children

Directions

pets 31 lbs and heavier | 5 sprays in mouth twice per day 5 days per week
pets 30 lbs and lighter | 3 sprays in mouth twice per day 5 days per week

- may be sprayed into pet's water bowl
- may be applied externally to the top of pet's head

Other Information

- do not use if plastic seal around cap is broken or missing.
- store in a cool, dry place.

Inactive Ingredients

Bird of Paradise*, Chin Cactus*, Desert Barrel Cactus*, Lemon*, Natural Flavor, Purified and Structured Water, Quaking Grass*, Rabbitbrush*, Rosa Californica*, Sweet Corn*

*flower essence

Questions or Comments?
Call 800.570.0021
Between 9am-5pm PST
info@siddhaflowers.com
siddhaflowers.com
Mfd for Siddha Flower Essences
Malibu, CA 90265
Made in USA

Side Panel

flower essences and homeopathy:

- Jump start your pet's natural ability to heal
- Natural, safe and non-habit forming
- No contraindications. May be effectively used with drugs and other supplements
- Alcohol, sugar, dairy and gluten free
- Prepared in purified and structured water with natural preservatives
- Blends time-tested natural medicine with modern technology
- 4 - 6 week supply depending on pet's weight

siddha pets
calm down
abandonment and separation
temperament and boundaries
oral health

Principal Display Panel

100% natural - no alcohol
siddha cell salts + flower essences
pets

temperament and boundaries
Angry Disposition
Easily Excitable
Timid and Afraid
Homeopathic Remedy
1 US fl oz (29.6mL)